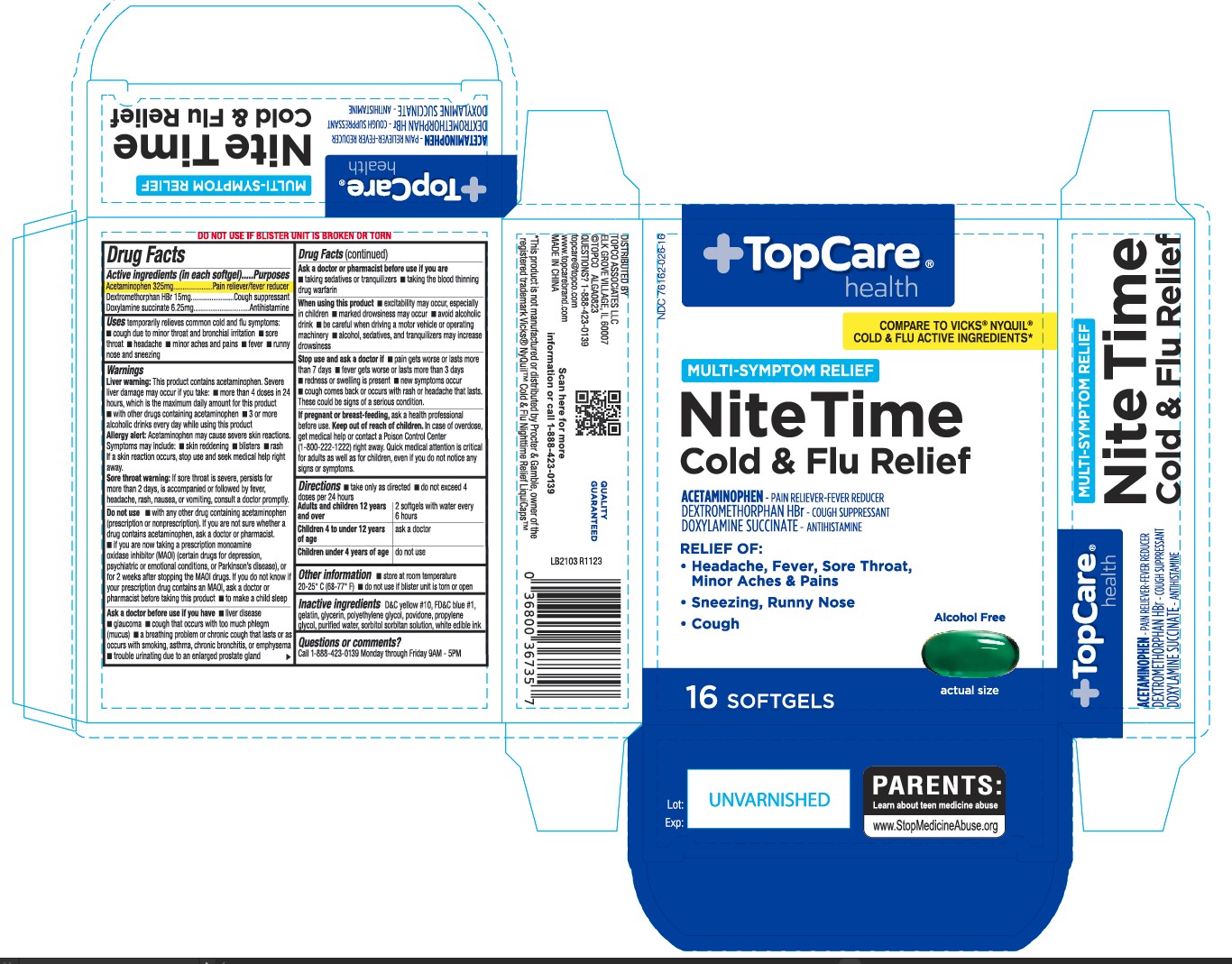 DRUG LABEL: Nite Time Cold and Flu Relief
NDC: 76162-026 | Form: CAPSULE, LIQUID FILLED
Manufacturer: TopCo Associates, LLC
Category: otc | Type: HUMAN OTC DRUG LABEL
Date: 20231031

ACTIVE INGREDIENTS: ACETAMINOPHEN 325 mg/1 1; DEXTROMETHORPHAN HYDROBROMIDE 15 mg/1 1; DOXYLAMINE SUCCINATE 6.25 mg/1 1
INACTIVE INGREDIENTS: D&C YELLOW NO. 10; FD&C BLUE NO. 1; GELATIN; GLYCERIN; POLYETHYLENE GLYCOL, UNSPECIFIED; POVIDONE; PROPYLENE GLYCOL; WATER; SORBITOL SOLUTION

418 - NiteTime Cold and Flu Relief

Active ingredient(s)

Acetaminophen 325mg
Dextromethorphan HBr 15mg
Doxylamine succinate 6.25mg

Purpose

Pain reliever/fever reducer
Cough suppressant
Antihistamine

Use(s)

temporarily relieves common cold/flu symptoms:
• cough due to minor throat & bronchial irritation • sore throat • headache
• minor aches & pains • fever • runny nose & sneezing

Warnings

Liver warning: This product contains acetaminophen.
Severe liver damage may occur if you take:
• more than 4 doses in 24 hrs, which is the maximum daily amount for this product
• with other drugs containing acetaminophen
• 3 or more alcoholic drinks every day while using this product

Allergy Alert: Acetaminophen may cause severe skin reactions.
Symptoms may include: • skin reddening • blisters • rash
If a skin reaction occurs, stop use and seek medical help right away.

Sore throat warning: If sore throat is severe, persists for more than 2 days,
occurs with or is followed by fever, headache, rash, nausea, or vomiting,
consult a doctor promptly.

Do not use

• with any other drug containing acetaminophen (prescription or
nonprescription). If you are not sure whether a drug contains acetaminophen,
ask a doctor or pharmacist.
• if you are now taking a prescription monoamine oxidase inhibitor (MAOI) (certain
drugs for depression, psychiatric or emotional conditions, or Parkinson's disease),
or for 2 weeks after stopping the MAOI drug. If you do not know if your prescription
drug contains an MAOI, ask a doctor or pharmacist before taking this product.
• to make a child sleep

Ask a doctor before use if

• liver disease

•glaucoma

• cough that occurs with too much phlegm (mucus)

• a breathing problem or chronic cough that lasts or as occurs with smoking, asthma, chronic bronchitis or emphysema

• trouble urinating due to enlarged prostate gland

Ask a doctor or pharmacist before use if

• taking sedatives or tranquilizers
• taking the blood thinning drug warfarin

When using this product

• do not use more than directed
• excitability may occur, especially in children
• marked drowsiness may occur • avoid alcoholic drinks
• be careful when driving a motor vehicle or operating machinery
• alcohol, sedatives & tranquilizers may increase drowsiness

Stop use and ask a doctor if

• pain or cough gets worse or lasts more than 7 days
• fever gets worse or lasts more than 3 days
• redness or swelling is present • new symptoms occur
• cough comes back or occurs with rash or headache that lasts.
These could be signs of a serious condition.

If pregnant or breastfeeding,

ask a health professional before use.

Keep out of reach of children

In case of overdose, get medical help or contact a Poison Control Center
(1-800-222-1222) right away. Quick medical attention is critical
for adults as well as for children, even if you do not notice any
signs or symptoms.

Directions

- take only as directed
- do not exceed 4 doses per 24 hours

Adults and children 12 years and over: 2 softgels with water every 6 hours

Children 4 to under 12 years of age: ask a doctor

Children under 4 years of age: do not use

Other information

- store at room temperature 20-25 °C (68-77° F)
- do not use if blister unit is torn or open

Inactive ingredients

D&C yellow #10, FD&C blue #1, gelatin, glycerin, polyethylene glycol, povidone, propylene
glycol, purified water, sorbitol sorbitan solution, white edible ink

Questions/Comments

Call 1-888-952-0050 Monday through Friday 9AM - 5PM

Principal Display Panel

Nitetime Cold and Flu